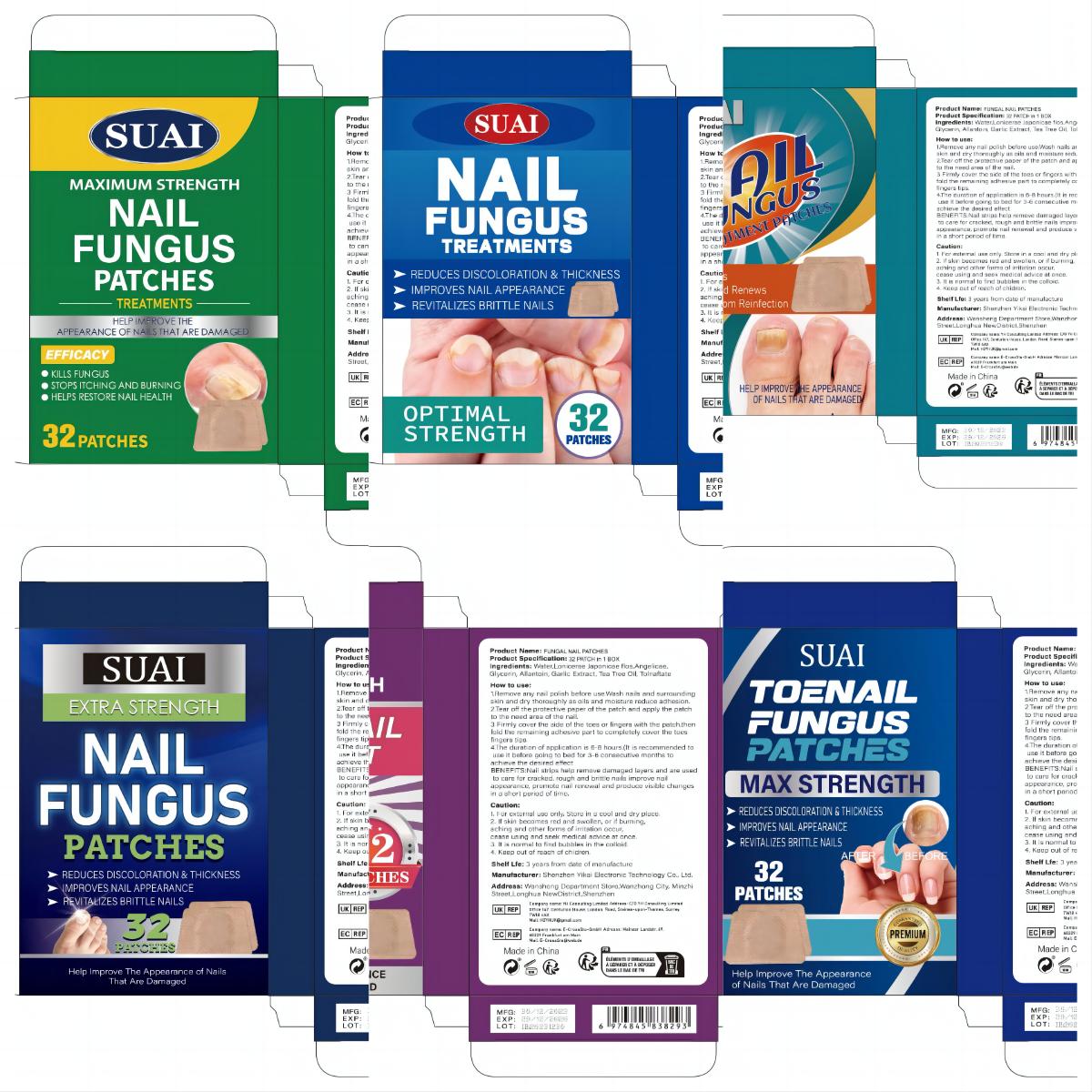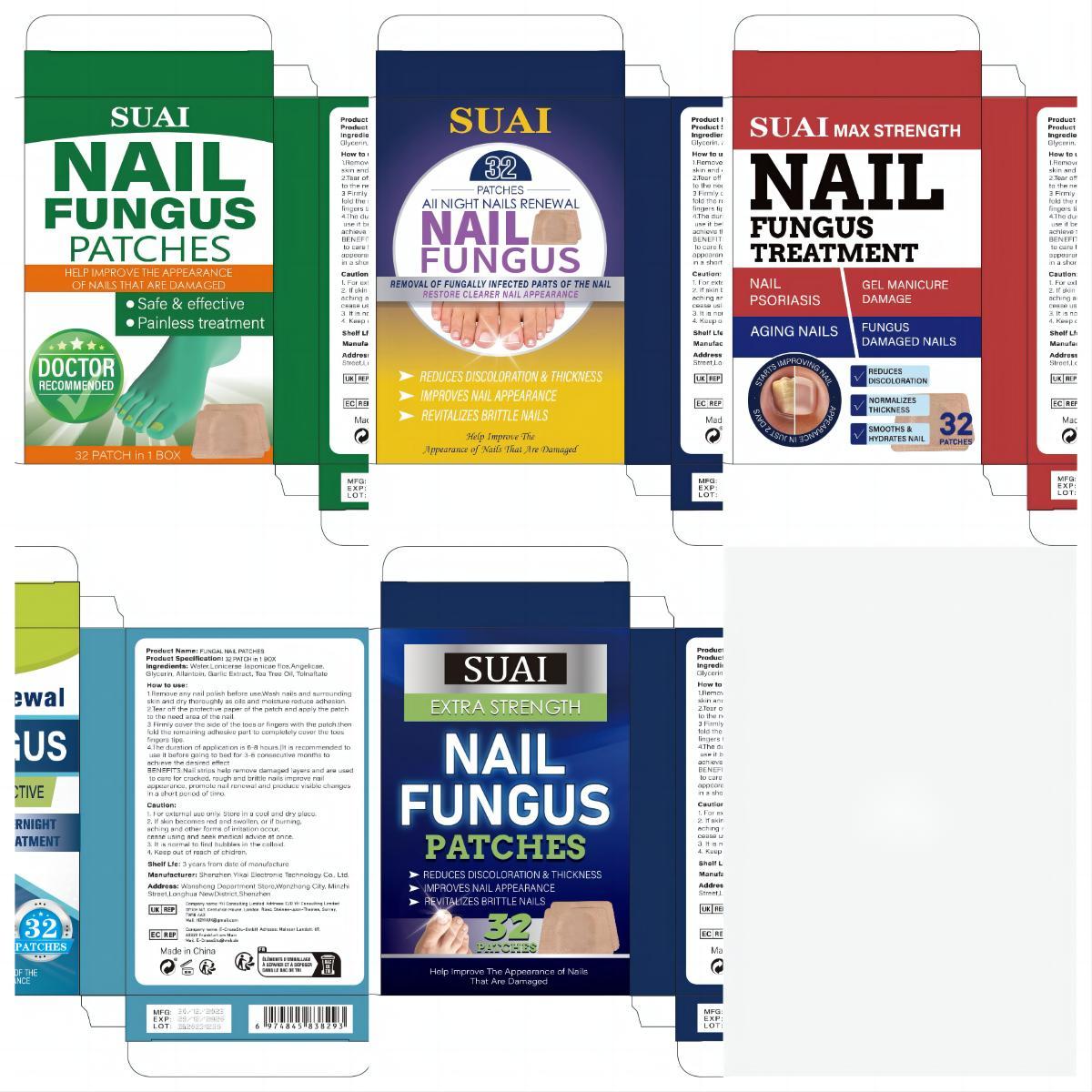 DRUG LABEL: FUNGAL NAIL PATCHES
NDC: 83809-021 | Form: PATCH
Manufacturer: Shenzhen Yikai Electronic Technology Co., Ltd.
Category: otc | Type: HUMAN OTC DRUG LABEL
Date: 20240613

ACTIVE INGREDIENTS: TOLNAFTATE 1 g/100 1
INACTIVE INGREDIENTS: TEA TREE OIL; WATER; LONICERA JAPONICA FLOWER; ANGELICA SINENSIS ROOT; GLYCERIN; ALLANTOIN; GARLIC

83809-021

Active Ingredient

Tolnaftate 1%

Purpose

Anti-fungal

Use

1.Remove any nail polish before use.Wash nails and surrounding skin and dry thoroughly as oils and moisture reduce adhesion.
2.Tear off the protective paper of the patch and apply the patch to the need area of the nail.
3 Firmly cover the side of the toes or fingers with the patch.then fold the remaining adhesive part to completely cover the toes fingers tips.
4.The duration of application is 6-8 hours.(lt is recommended to use it before going to bed for 3-6 consecutive months to achieve the desired effect.

Warnings

1. For external use only. Store in a cool and dry place.
2. If skin becomes red and swollen, or if burning, aching and other forms of irritation occur, cease using and seek medical advice at once.
3. It is normal to find bubbles in the colloid.
4. Keep out of reach of children.

Stop Use

This product has not been found allergic. If allergic occurs, stop using it immediately.

Keep Oot Of Reach Of Children

Please store this product out of the reach of children

Directions

Please wipe your skin clean before use and apply it gently to the affected area.

Inactive ingredients

Water,Lonicerae Japonicae flos,Angelicae,Glycerin, Allantoin, Garlic Extract, Tea Tree Oil